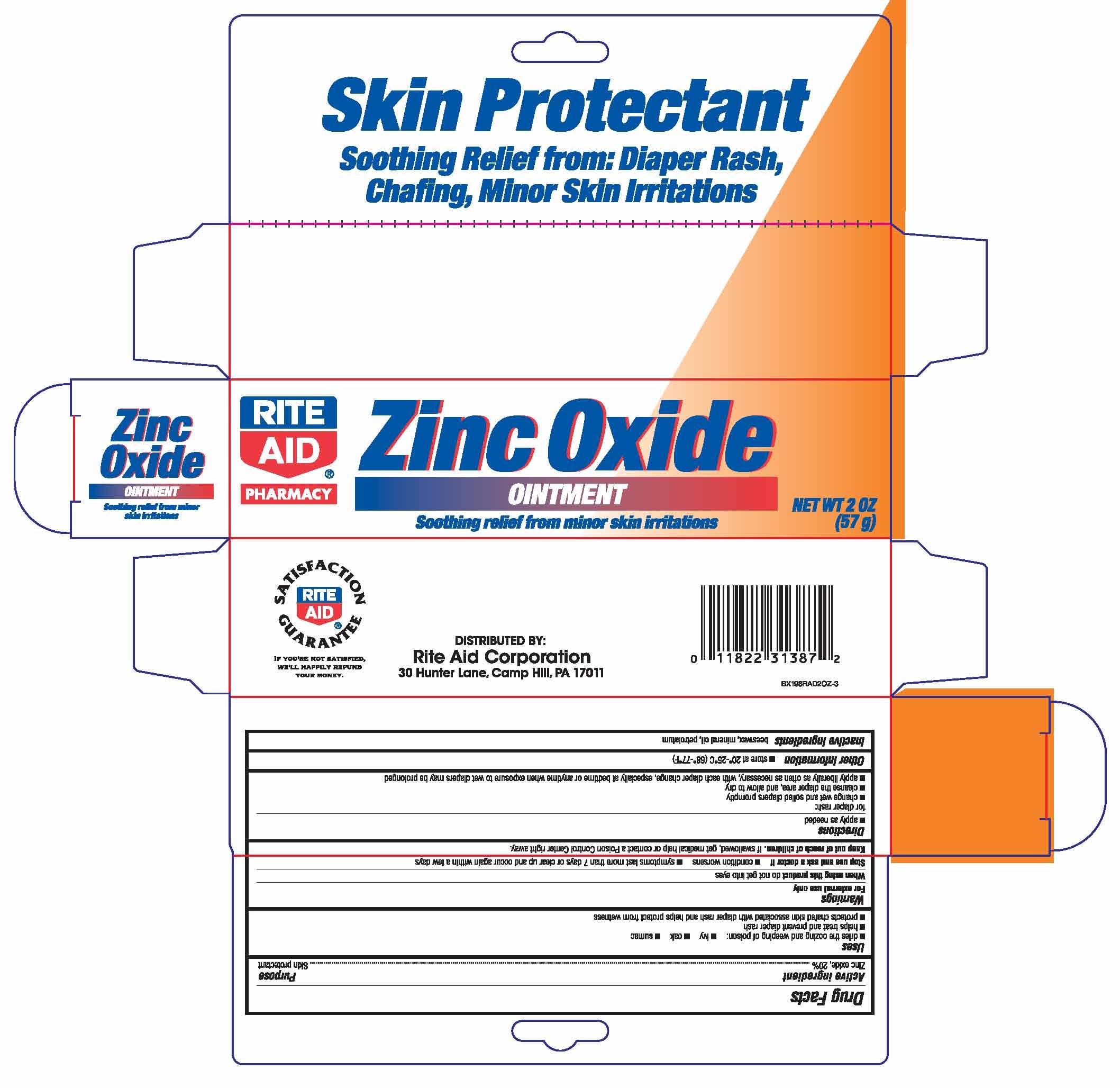 DRUG LABEL: ZINC OXIDE
NDC: 11822-0081 | Form: OINTMENT
Manufacturer: RiteAid
Category: otc | Type: HUMAN OTC DRUG LABEL
Date: 20110216

ACTIVE INGREDIENTS: ZINC OXIDE 200 mg/1 g
INACTIVE INGREDIENTS: PETROLATUM; WHITE WAX; LIGHT MINERAL OIL

drug facts

Active ingredient Purpose
Zinc Oxide........................................Skin protectant

Active ingredient Purpose
Zinc Oxide.................................Skin protectant
Uses
- dries the oozing and weeping od poison - ivy - oak - sumac
- helps treat and prevent diaper rash
- protects chafed skin associated with diaper rash and helps protect from wetness

Keep out of the reach of children.
If swallowed, get medical help or contact
a Poison Control Center right away.

Uses
- dries the oozing and weeping od poison - ivy - oak - sumac
- helps treat and prevent diaper rash
- protects chafed skin associated with diaper rash and helps protect from wetness

Warnings
For external use only.
When using this product do not get into eyes
Stop use and ask a doctor if:
- condition worsens - symptoms last more than 7 days or clear
up and occur again within a few days.
Keep out of the reach of children. If swallowed get medical help or contact a Poison Control Center right away

Directions
- apply as needed
For diaper rash
- change wet and soiled diapers promptly
- cleanse the diaper area, and allow to dry
- apply liberally as often as necessary, with each diaper change,
especially at bedtime or anytime when exposure to wet diapers may be prolonged
- children under 12 years
ask a doctor
Other information
Store at 20 degrees to 25 degrees C (68 degrees to 77 degrees F)

Inactive Ingredients
beeswax, mineral oil, petrolatum